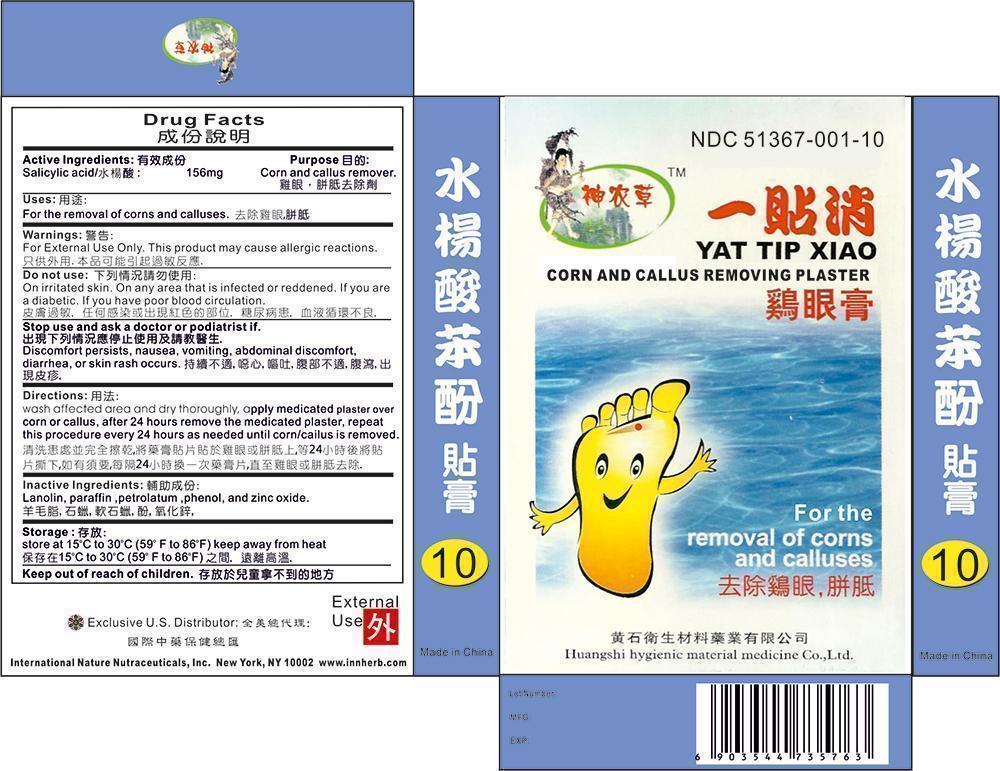 DRUG LABEL: Yat Tip Xiao
                
                
NDC: 51367-001 | Form: PLASTER
Manufacturer: Internationa Nature Nutraceuticals, Inc
Category: otc | Type: HUMAN OTC DRUG LABEL
Date: 20171222

ACTIVE INGREDIENTS: Salicylic Acid 156 mg/1 1
INACTIVE INGREDIENTS: Lanolin; Paraffin; Petrolatum; Phenol; Zinc Oxide

Drug Facts

Active Ingredients

Salicylic Acid 156mg

Purpose

Corns and callus remover

Warnings

For external use only. This product may cause allergic reactions.

Stop use and ask doctor or podiatrist if

Discomfort persists, nausea, vomiting, abdominal discomfort, diarrhea, or skin rash occurs

Do not use

On irritated skin. On an area that is reddened or infected. If you are a diabetic. If you have poor blood circulation

Keep out of reach of children

Storage

Store at 15-30 degrees C. Keep away from heat.

Use

For the removal of corns and callus

Directions

Wash affected area and dry throughly, apply medicated plaster over corns and calluses, after 24 hours remove the medicated plaster, repeat this procedure every 24 hours as needed until corn /callus is removed

Inactive Ingredients

Lanolin, paraffin, petrolatum, phenol, and zinc oxide